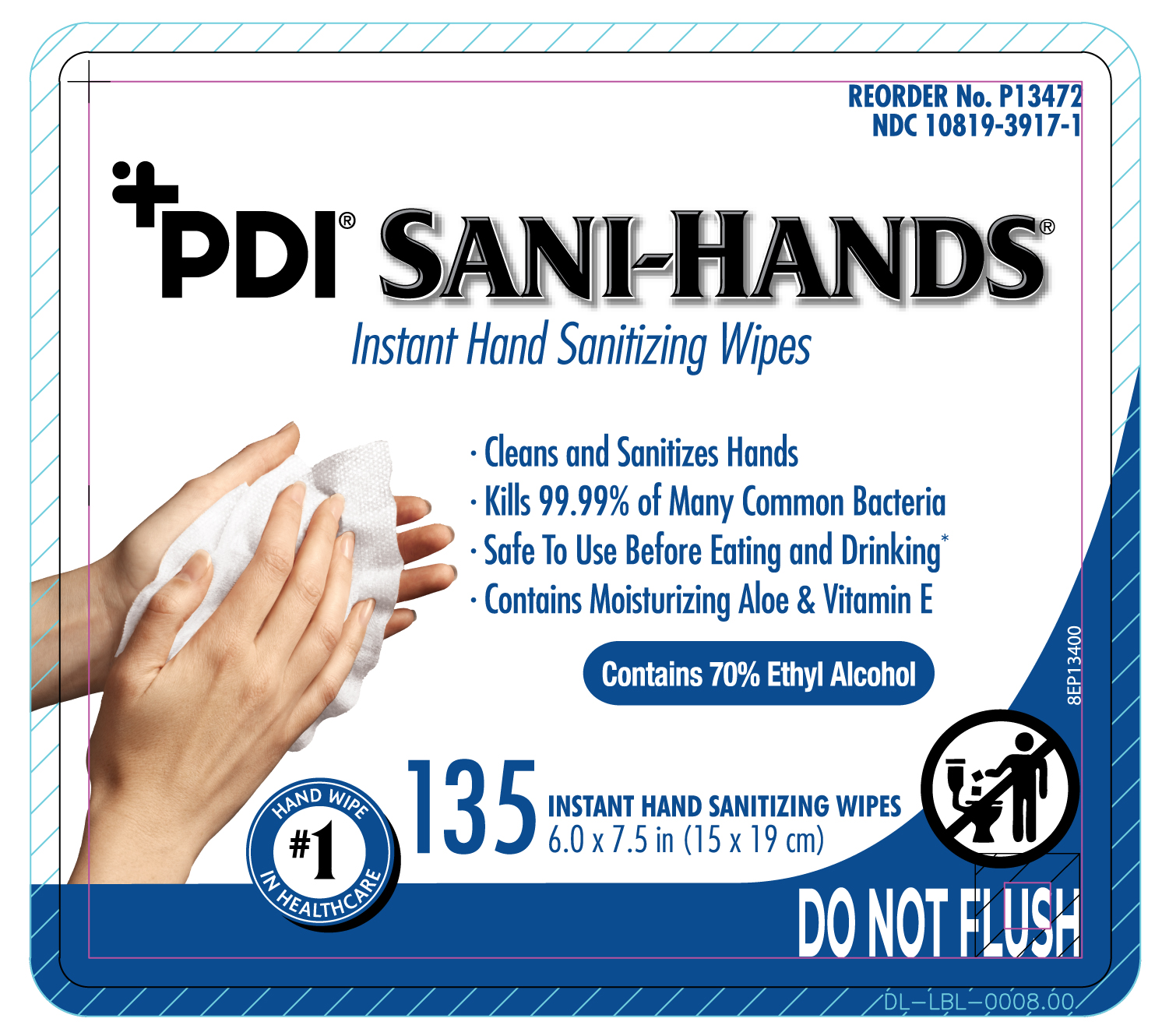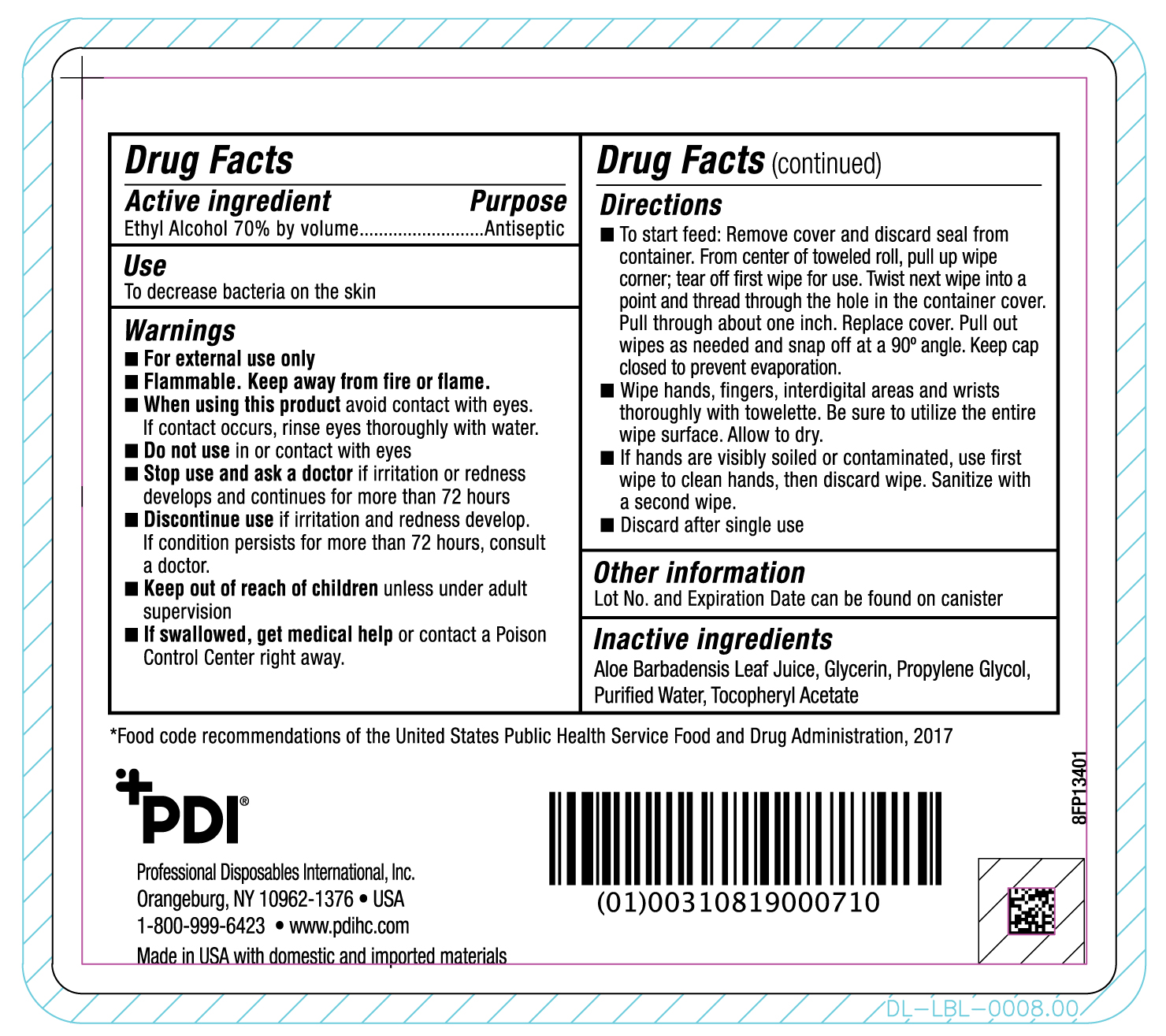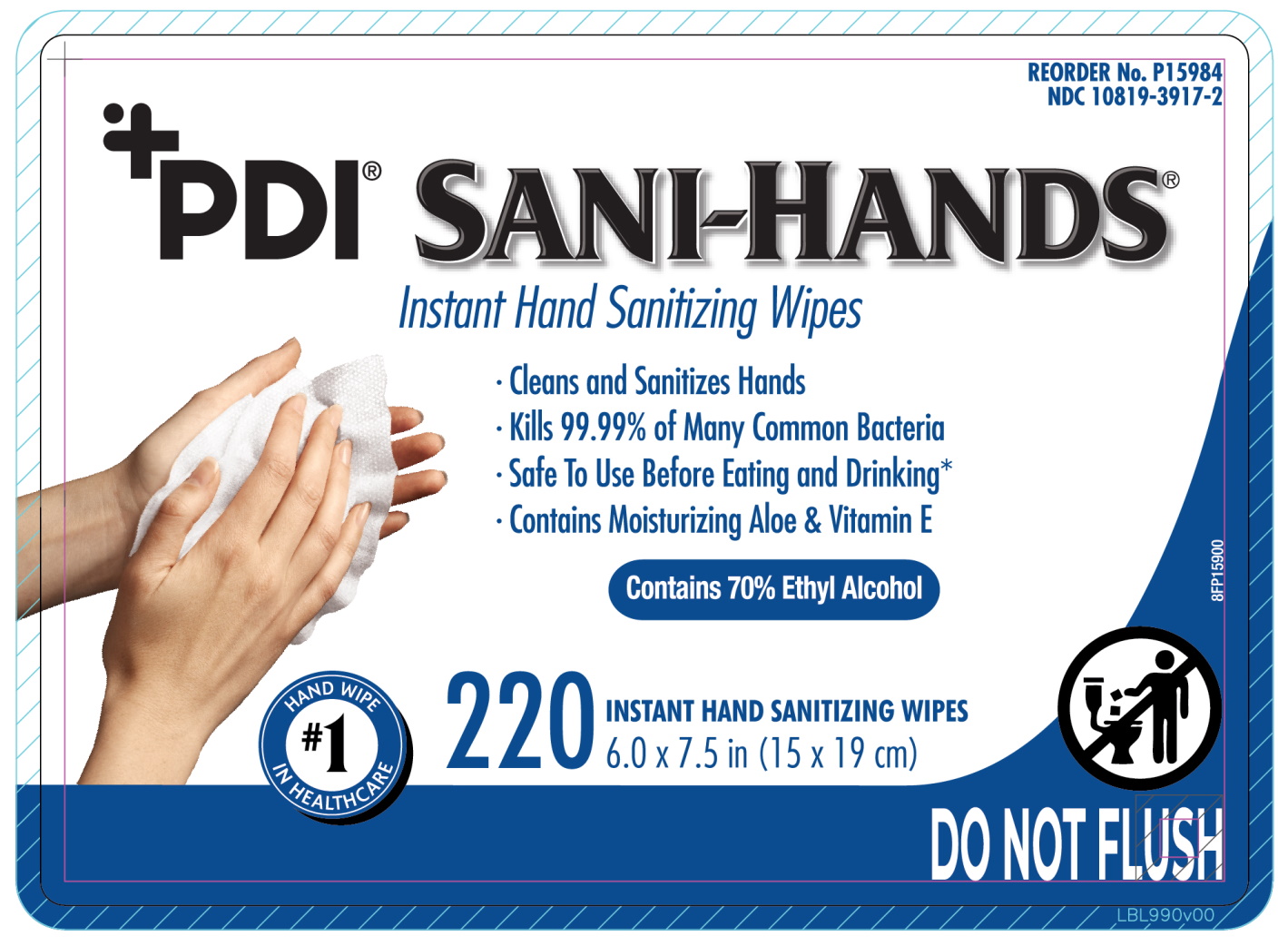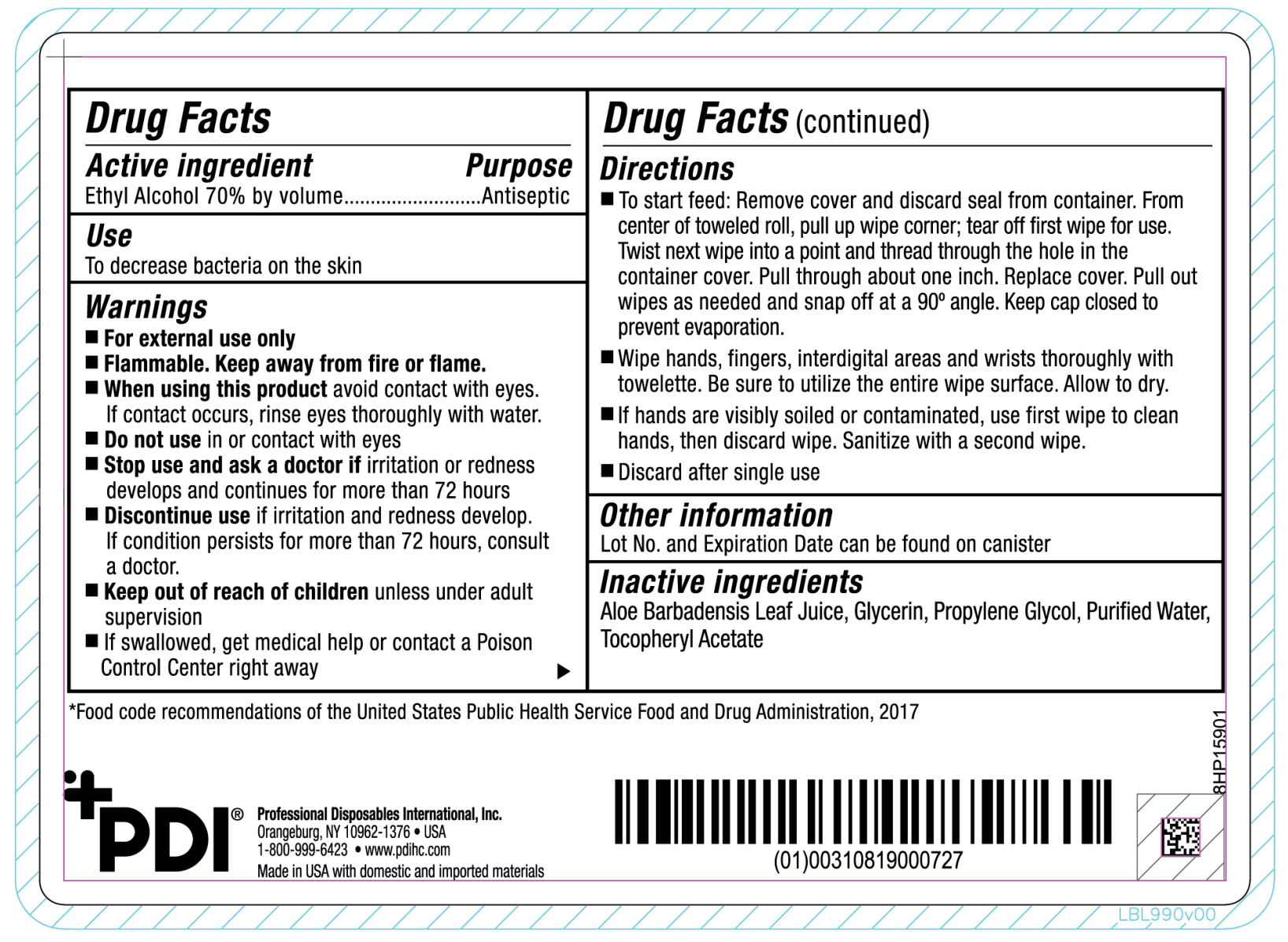 DRUG LABEL: PDI Sani-Hands
NDC: 10819-3917 | Form: CLOTH
Manufacturer: Professional Disposables International, Inc.
Category: otc | Type: HUMAN OTC DRUG LABEL
Date: 20240820

ACTIVE INGREDIENTS: ALCOHOL 0.659 mL/1 mL
INACTIVE INGREDIENTS: WATER; PROPYLENE GLYCOL; GLYCERIN; ALOE VERA LEAF; ALPHA-TOCOPHEROL ACETATE

PDI SANI-HANDS INSTANT HAND SANITIZING WIPES

Uses

To decrease bacteria on the skin

Warnings

- For external use only
- Flammable. Keep away from fire or flame.
- When using this product avoid contact with eyes. If contact occurs, rinse eyes thoroughly with water
- Do not use in or contact with eyes.
- Stop use and ask a doctor if irritation or redness develops and continues for more than 72 hours
- Discontinue use if irritation and redness develop. If condition for more persists for more than 72 hours, consult a doctor

Inactive ingredients

aloe barbadensis leaf juice, glycerin, propylene glycol, purified water, tocopheryl acetate

Active ingredient

Alcohol 70% by volume

Purpose

Antiseptic

Keep out of reach of children unless under adult supervision.

If swallowed, get medical help or contact a Poison Control Center right away

Directions

- To start feed: Remove cover and discard seal from container. From center of toweled roll, pull up wipe corner; tear off first wipe for use. Twist next wipe into a point and thread through the hole in the container cover. Pull through about one inch. Replace cover. Pull out wipes as needed and snap off at a 90o angle. Keep cap closed to prevent evaporation.

- Wipe hands, fingers, interdigital areas and wrists thoroughly with towelette. Be sure to utilize the entire wipe surface. Allow to dry.

- If hands are visibly soiled or contaminated, use first wipe to clean hands, then discard wipe. Sanitize with a second wipe.

- Discard after single use.

Other information

Lot No. and Expiration Date can be found on canister.

Principal Display Panel

front 135 ct

back 135ct

front 220 ct

back 200 ct